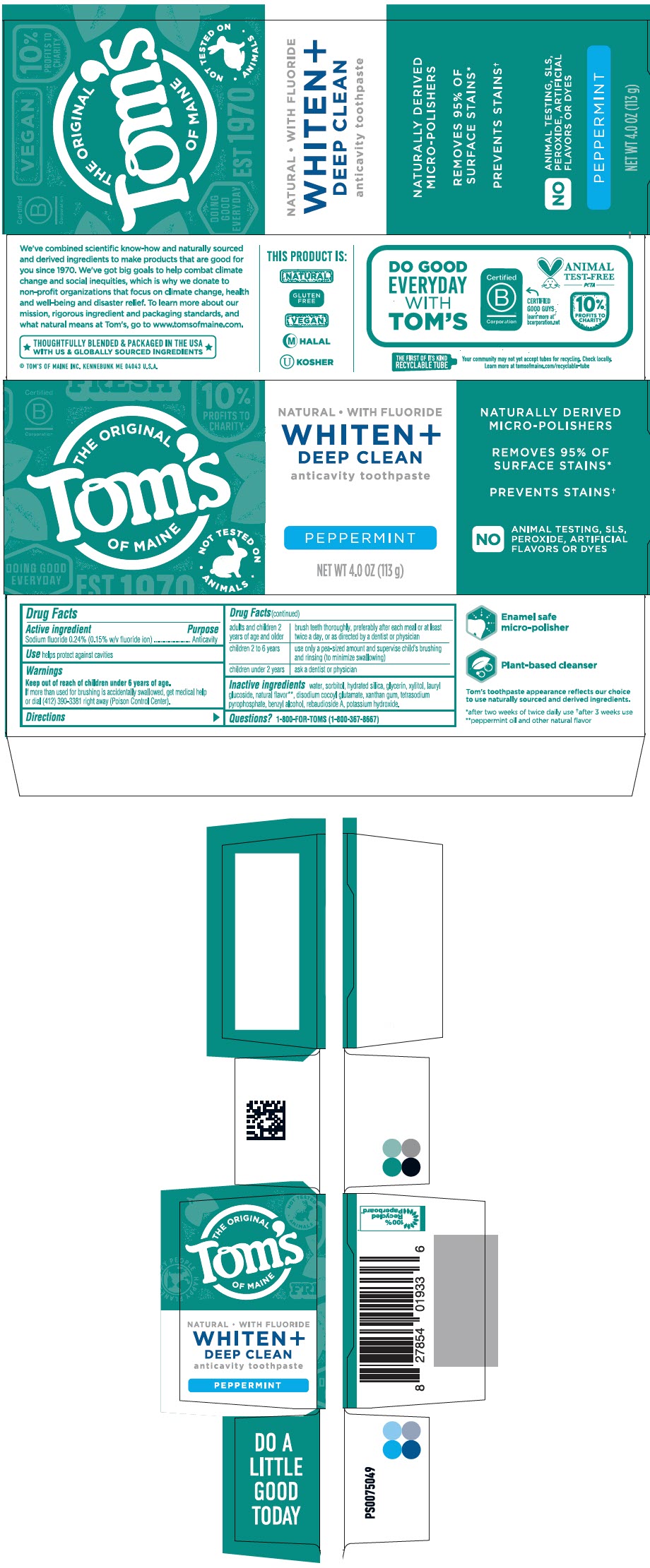 DRUG LABEL: Toms of Maine Whiten Plus Deep Clean Peppermint
NDC: 51009-920 | Form: PASTE, DENTIFRICE
Manufacturer: Tom's of Maine
Category: otc | Type: HUMAN OTC DRUG LABEL
Date: 20260218

ACTIVE INGREDIENTS: SODIUM FLUORIDE 1.1 mg/1 g
INACTIVE INGREDIENTS: WATER; SORBITOL; HYDRATED SILICA; GLYCERIN; XYLITOL; LAURYL GLUCOSIDE; PEPPERMINT OIL; DISODIUM COCOYL GLUTAMATE; XANTHAN GUM; SODIUM PYROPHOSPHATE; BENZYL ALCOHOL; REBAUDIOSIDE A; POTASSIUM HYDROXIDE

Tom's of Maine Whiten + Deep Clean Peppermint

Drug Facts

Active ingredient

Sodium fluoride 0.24% (0.15% w/v fluoride ion)

Purpose

Anticavity

Use

helps protect against cavities

Warnings

Keep out of reach of children under 6 years of age.

If more than used for brushing is accidentally swallowed, get medical help or dial (412) 390-3381 right away (Poison Control Center).

Directions

adults and children 2 years of age and older | brush teeth thoroughly, preferably after each meal or at least twice a day, or as directed by a dentist or physician
children 2 to 6 years | use only a pea-sized amount and supervise child's brushing and rinsing (to minimize swallowing)
children under 2 years | ask a dentist or physician

Inactive ingredients

water, sorbitol, hydrated silica, glycerin, xylitol, lauryl glucoside, natural flavor [peppermint oil and other natural flavor] , disodium cocoyl glutamate, xanthan gum, tetrasodium pyrophosphate, benzyl alcohol, rebaudioside A, potassium hydroxide.

Questions?

1-800-FOR-TOMS (1-800-367-8667)

PRINCIPAL DISPLAY PANEL - 113 g Tube Carton

THE ORIGINAL
Tom's
OF MAINE

• NOT TESTED ON •
ANIMALS

NATURAL • WITH FLUORIDE

WHITEN +
DEEP CLEAN

anticavity toothpaste

PEPPERMINT

NET WT 4.0 OZ (113 g)

NATURALLY DERIVED
MICRO-POLISHERS

REMOVES 95% OF
SURFACE STAINS*

PREVENTS STAINS†

NO
ANIMAL TESTING, SLS,
PEROXIDE, ARTIFICIAL
FLAVORS OR DYES